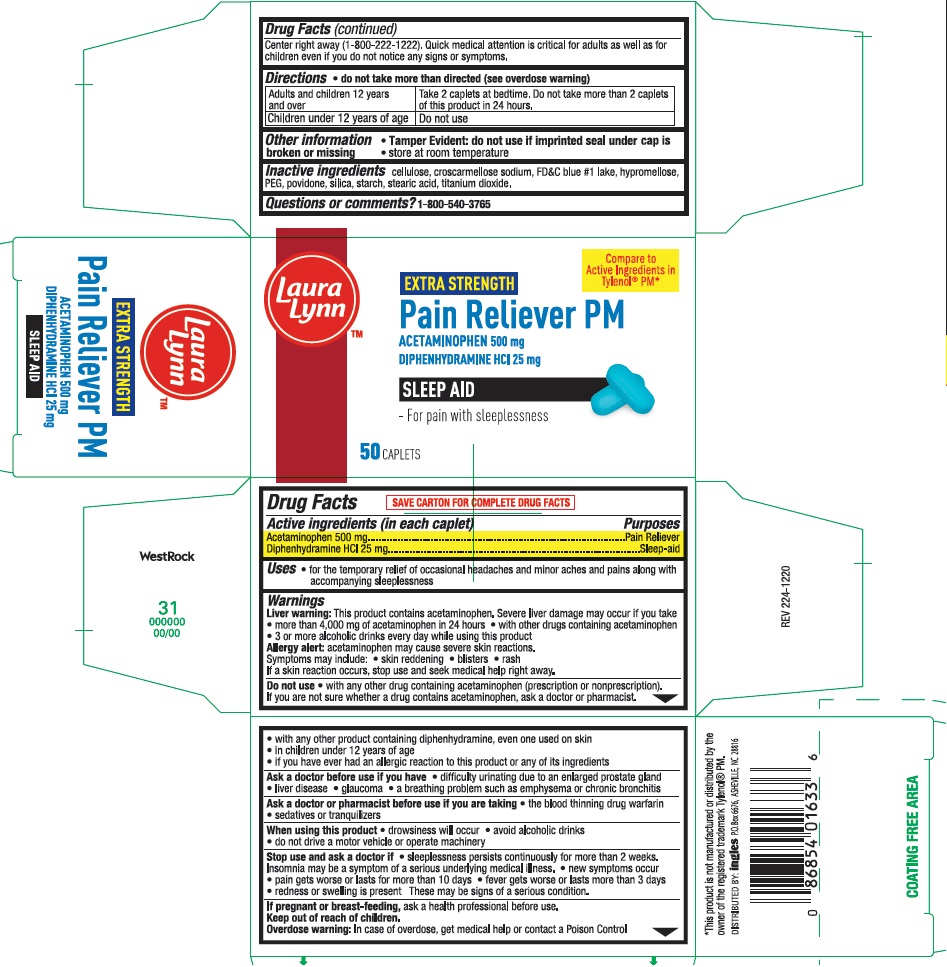 DRUG LABEL: Extra Strength  Pain Reliever PM
NDC: 62936-0224 | Form: TABLET
Manufacturer: INGLES MARKETS, INC.
Category: otc | Type: HUMAN OTC DRUG LABEL
Date: 20241128

ACTIVE INGREDIENTS: ACETAMINOPHEN 500 mg/1 1; DIPHENHYDRAMINE HYDROCHLORIDE 25 mg/1 1
INACTIVE INGREDIENTS: STARCH, CORN; POVIDONE; FD&C BLUE NO. 1; CROSCARMELLOSE SODIUM; HYPROMELLOSES; CELLULOSE, MICROCRYSTALLINE; POLYETHYLENE GLYCOL, UNSPECIFIED; STEARIC ACID; TITANIUM DIOXIDE; SILICON DIOXIDE

lly 224

Active Ingredients

Acetaminophen 500 mg

Diphenhydramine HCI 25 mg

Purposes

Pain Reliever

Sleep aid

Uses

for the temporary relief of occasional headaches and minor aches and pains along with accompanying sleeplessness

Warnings

Liver warning: This product contains acetaminophen. Severe liver damage may occur if you take

- more than 4,000 mg of acetaminophen in 24 hours
- with other drugs containing acetaminophen
- 3 or more alcoholic drinks every day while using this product

Allergy alert: acetaminophen may cause severe skin reactions.

Symptoms may include: • skin reddening • blisters • rash
If a skin reaction occurs, stop use and seek medical help right away.

Do not use • with any other drug containing acetaminophen (prescription or
nonprescription). If you are not sure whether a drug contains acetaminophen,
ask a doctor or pharmacist. • with any other product containing
diphenhydramine, even one used on skin • in children under 12 years of age
• if you have ever had an allergic reaction to this product or any of its ingredients

Ask a doctor before use if you have • liver disease • a breathing problem such as emphysema or chronic bronchitis • glaucoma • difficulty urinating due to an enlarged prostate gland

Ask a doctor or pharmacist before use if you are taking • the blood thinning drug warfarin

• sedatives or tranquilizers

When using this product • drowsiness will occur • do not drive a motor vehicle or operate machinery after use • avoid alcoholic drinks

Stop use and ask a doctor if • sleeplessness persists continuously for more than 2 weeks. Insomnia may be a symptom of a serious underlying medical illness. • pain gets worse or lasts for more that 10 days • fever gets worse or lasts more than 3 days • new symptoms occur • redness or swelling is present.These may be signs of a serious condition.

If pregnant or breast-feeding, ask a health professional before use.

Keep out of reach of children.
Overdose warning: In case of overdose, get medical help or contact a Poison
Control Center right away. (1-800-222-1222). Quick medical attention is critical for
adults as well as for children even if you do not notice any signs or symptoms.

Directions

• do not take more than directed (see overdose warning)

Adults and Children 12 years and over | Take 2 caplets at bedtime. Do not take more than 2 caplets of this product in 24 hours.
Children under 12 years | Do not use.

Other information

• store at room temperature

Inactive ingredients

croscarmellose sodium, FD&C blue #1 lake, hypromellose, microcrystalline cellulose, PEG, povidone, silica, starch, stearic acid, titanium dioxide

Questions or comments?

1-800-540-3765